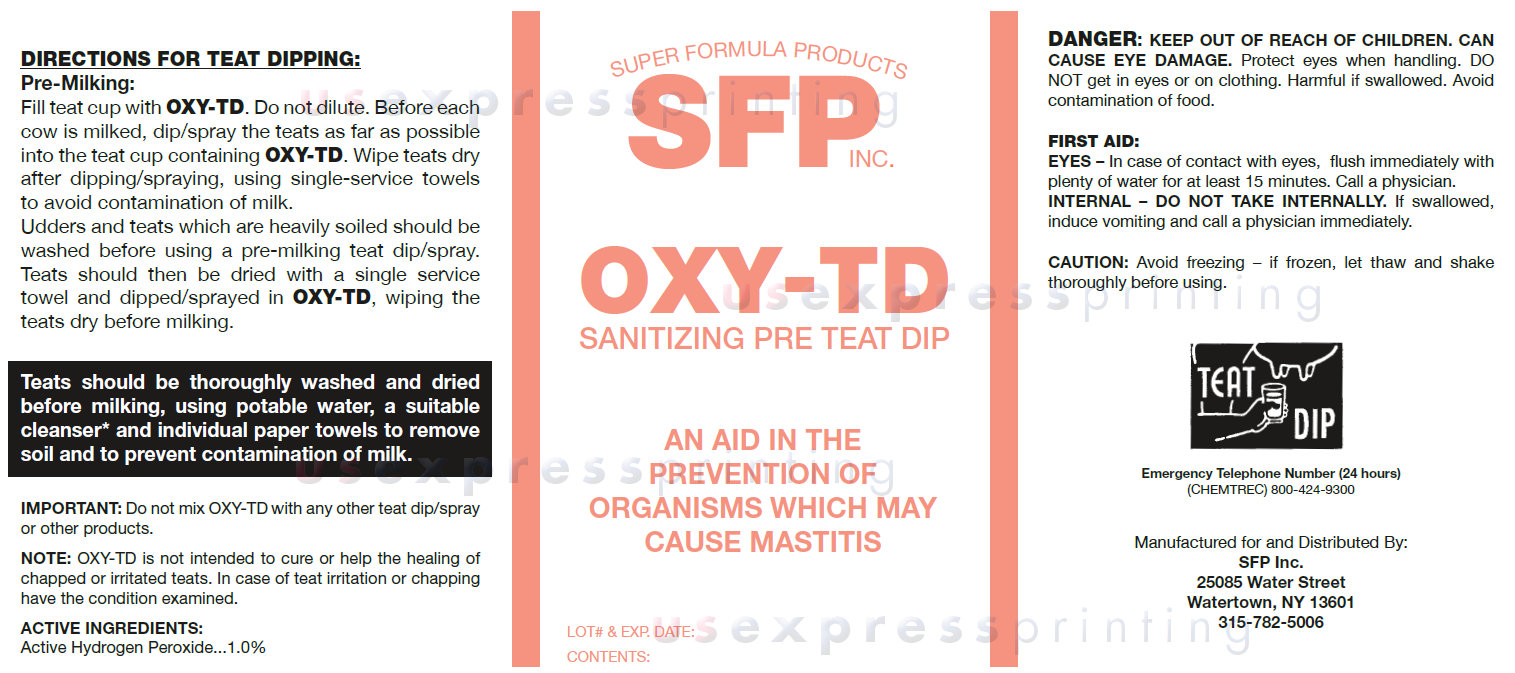 DRUG LABEL: SFP INC. OXY-TD SANITIZING PRE TEAT DIP
NDC: 35723-100 | Form: LIQUID
Manufacturer: SUPER FORMULA PRODUCTS INC.
Category: animal | Type: OTC ANIMAL DRUG LABEL
Date: 20140723

ACTIVE INGREDIENTS: HYDROGEN PEROXIDE 1.0 L/100 L

SFP INC. OXY-TD SANITIZING PRE TEAT DIP

DIRECTIONS FOR TEAT DIPPING:

Pre-Milking:
Fill teat cup with OXY-TD. Do not dilute. Before each cow is milked, dip/spray the teats as far as possible into the teat cup containing OXY-TD. Wipe teats dry after dipping/spraying, using single-service towels to avoid contamination of milk.
Udders and teats which are heavily soiled should be washed before using a pre-milking teat dip/spray. Teats should then be dried with a single service towel and dipped/sprayed in OXY-TD, wiping the teats dry before milking.
Teats should be thoroughly washed and dried before milking, using potable water, a suitable cleanser* and individual paper towels to remove soil and to prevent contamination of milk.
IMPORTANT: Do not mix OXY-TD with any other teat dip/spray or other products.
NOTE: OXY-TD is not intended to cure or help the healing of chapped or irritated teats. In case of teat irritation or chapping have the condition examined.

ACTIVE INGREDIENTS:

Active Hydrogen Peroxide...1.0%

WARNINGS AND PRECAUTIONS

DANGER: Keep Out Of Reach Of Children. Can Cause Eye Damage. Protect eyes when handling. DO NOT get in eyes or on clothing. Harmful if swallowed. Avoid contamination of food.
FIRST AID:
EYES – In case of contact with eyes, flush immediately with plenty of water for at least 15 minutes. Call a physician.
INTERNAL – DO NOT TAKE INTERNALLY. If swallowed, induce vomiting and call a physician immediately.
CAUTION: Avoid freezing – if frozen, let thaw and shake thoroughly before using.